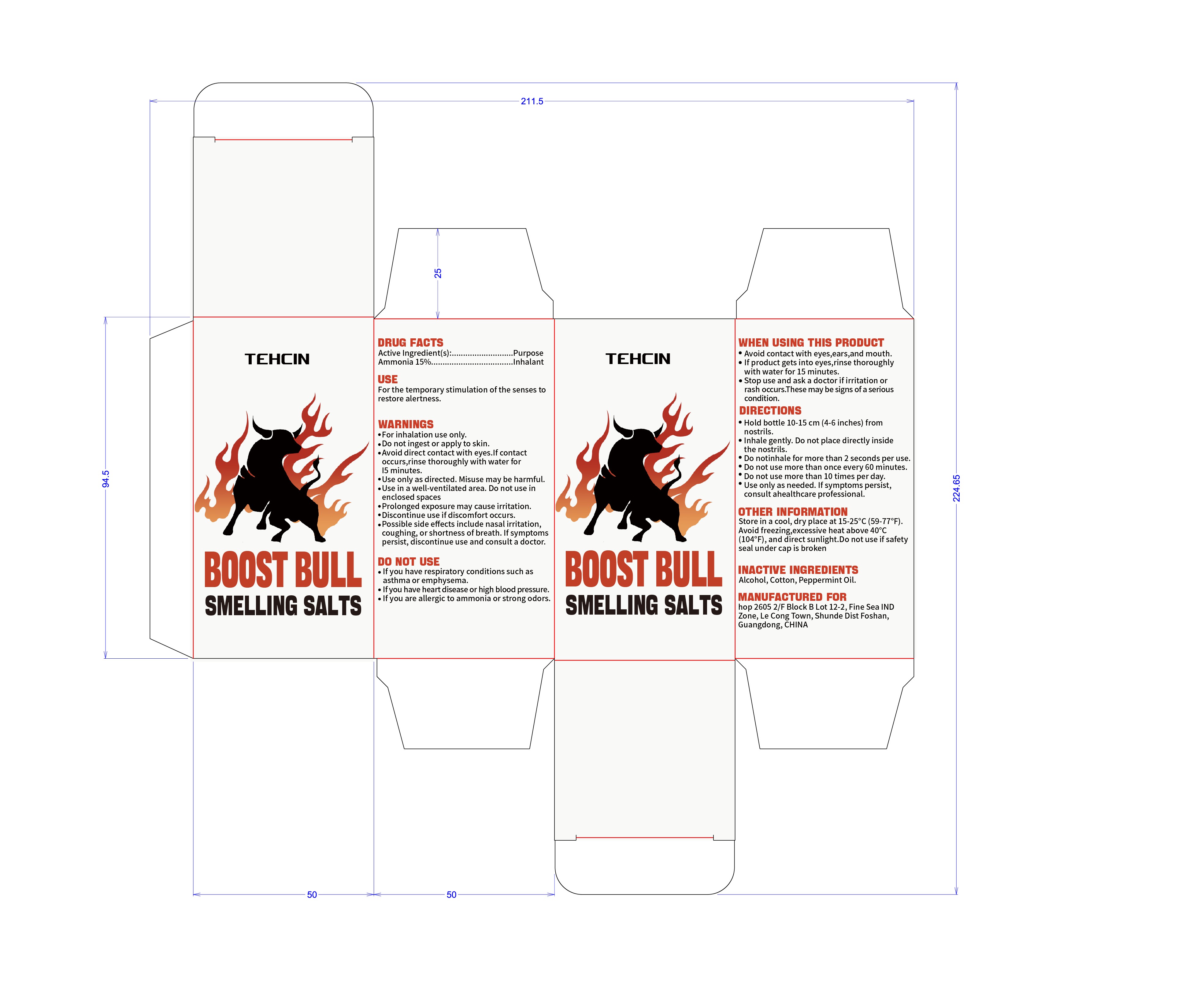 DRUG LABEL: TEHCIN smelling salts
NDC: 85593-117 | Form: INHALANT
Manufacturer: Guangzhou ChuanMa International Trading Co.,Ltd.
Category: otc | Type: HUMAN OTC DRUG LABEL
Date: 20251222

ACTIVE INGREDIENTS: AMMONIA 15 g/100 g
INACTIVE INGREDIENTS: ALCOHOL; COTTON; PEPPERMINT OIL

ACTIVE INGREDIENT

Ammonia 15%

Keep out of reach of children. If swallowed, get medical help or contact a Poison Control Center immediately at 1-800-222-1222.

PURPOSE

Inhalant For the temporary stimulation of the senses to restore alertness.

WARNINGS

Do not ingest or apply to skin.
Avoid direct contact with eyes. If contact occurs, rinse thoroughly with water for 15 minutes.
Use only as directed. Misuse may be harmful.
Use in a well-ventilated area. Do not use in enclosed spaces.
Prolonged exposure may cause irritation. Discontinue use if discomfort occurs.
Possible side effects include nasal irritation, coughing, or shortness of breath. If symptoms persist, discontinue use and consult a doctor.

DOSAGE AND ADMINISTRATION

Hold bottle 10-15 cm (4-6 inches) from nostrils.
Inhale gently. Do not place directly inside the nostrils.
Do not inhale for more than 2 seconds per use.
Do not use more than once every 60 minutes.
Do not use more than 10 times per day.
Use only as needed. If symptoms persist, consult a healthcare professional.

INACTIVE INGREDIENT

Alcohol, Cotton, Peppermint Oil.

INDICATIONS AND USAGE

Avoid contact with eyes, ears, and mouth.
If product gets into eyes, rinse thoroughly with water for 15 minutes.
Stop use and ask a doctor if irritation or rash occurs. These may be signs of a serious condition.